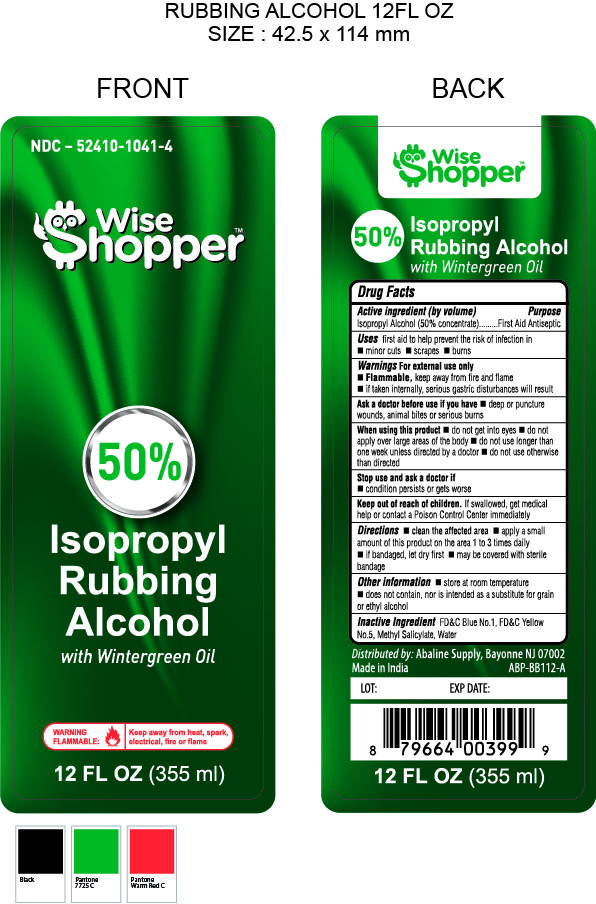 DRUG LABEL: WISE SHOPPER 50% ISOPROPYL RUBBING ALCOHOL W/ WINTERGREEN
NDC: 52410-1041 | Form: LIQUID
Manufacturer: Shield Line LLC
Category: otc | Type: HUMAN OTC DRUG LABEL
Date: 20210224

ACTIVE INGREDIENTS: ISOPROPYL ALCOHOL 50 mL/100 mL
INACTIVE INGREDIENTS: METHYL SALICYLATE; FD&C BLUE NO. 1; FD&C YELLOW NO. 5; WATER

WISE SHOPPER WINTERGREEN 50% IPA

Drug Facts

Isopropyl Alcohol (50% v/v)

Purpose

First Aid Antiseptic

Uses

first aid to help prevent the risk of infection in

- minor cuts
- scrapes
- burns

Warnings For external use only

- Flammable, keep away from fire and flame
- if taken internally, serious gastric disturbances will result

Ask a doctor before use if you have

- deep or puncture wounds, animal bites or serious burns

When using this product

- do not get into eyes
- do not apply over large areas of the body
- do not use longer than one week unless directed by a doctor
- do not use otherwise than directed

Stop use and ask a doctor if

- condition persists or gets worse

Keep out of reach of children

If swallowed , get medical help or contact a Poison Control Center immediately

DOSAGE AND ADMINISTRATION

- clean the affected area
- apply a small amount of this product on area 1 to 3 times daily
- if bandaged, let dry first
- may be covered with sterile bandage

Other information

- store at room temperature
- does not contain, nor is intended as a substitute for grain or ethyl alcohol

Inactive Ingredients

FD&C Blue No.1, FD&C Yellow No. 5, Methyl Salicylate, Water